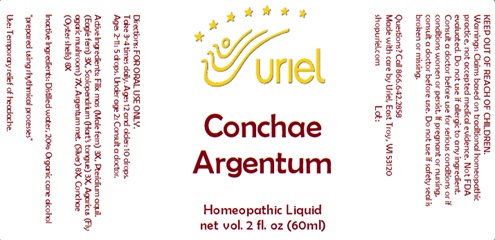 DRUG LABEL: Conchae Argentum
NDC: 48951-3258 | Form: LIQUID
Manufacturer: Uriel Pharmacy, Inc.
Category: homeopathic | Type: HUMAN OTC DRUG LABEL
Date: 20240118

ACTIVE INGREDIENTS: ASPLENIUM SCOLOPENDRIUM TOP 3 [hp_X]/1 mL; OSTREA EDULIS SHELL 8 [hp_X]/1 mL; SILVER 8 [hp_X]/1 mL; DRYOPTERIS FILIX-MAS ROOT 3 [hp_X]/1 mL; PTERIDIUM AQUILINUM WHOLE 3 [hp_X]/1 mL; AMANITA MUSCARIA FRUITING BODY 7 [hp_X]/1 mL
INACTIVE INGREDIENTS: ALCOHOL; WATER

Conchae Argentum

INDICATIONS AND USAGE

Directions: FOR ORAL USE ONLY.

DOSAGE AND ADMINISTRATION

Take 3-4 times daily. Ages 12 and older: 10 drops. Ages 2-11: 5 drops. Under age 2: Consult a doctor.

ACTIVE INGREDIENT

Active Ingredients: Filix mas (Male fern) 3X, Pteridium aquil. (Eagle fern) 3X, Scolopendrium (Hart’s tongue) 3X, Agaricus (Fly agaric mushroom) 7X, Argentum met. (Silver) 8X, Conchae (Oyster shells) 8X

Inactive Ingredients: Distilled water, 20% Organic cane alcohol

"prepared using rhythmical processes"

PURPOSE

Use: Temporary relief of headache

KEEP OUT OF REACH OF CHILDREN.

WARNINGS

Warnings: Claims based on traditional homeopathic practice, not accepted medical evidence. Not FDA evaluated. Do not use if allergic to any ingredient. Consult a doctor before use for serious conditions or if conditions worsen or persist. If pregnant or nursing, consult a doctor before use. Do not use if safety seal is broken or missing.

Questions? Call 866.642.2858
Made with care by Uriel, East Troy, WI 53120
shopuriel.com Lot: